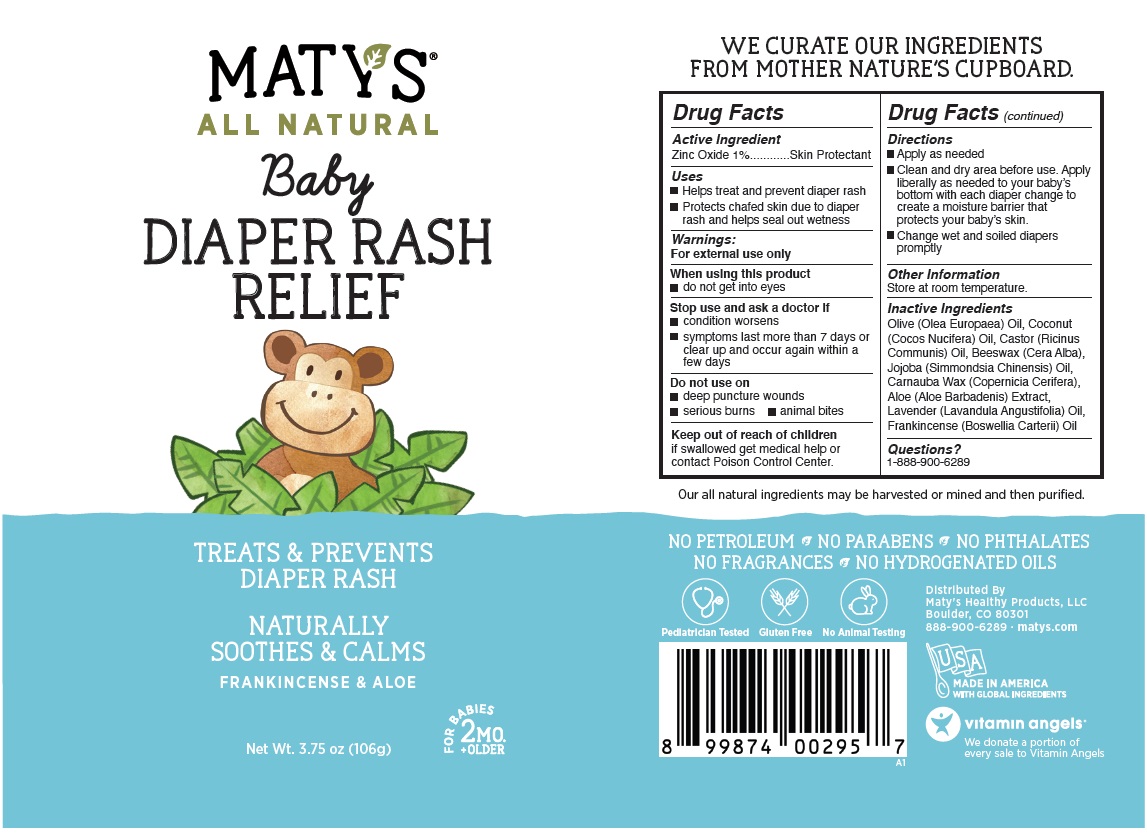 DRUG LABEL: MATYS Baby DIAPER RASH RELIEF
NDC: 72827-102 | Form: OINTMENT
Manufacturer: Matys Healthy Products LLC
Category: otc | Type: HUMAN OTC DRUG LABEL
Date: 20250129

ACTIVE INGREDIENTS: ZINC OXIDE 1 g/100 g
INACTIVE INGREDIENTS: OLIVE OIL; COCONUT OIL; CASTOR OIL; YELLOW WAX; JOJOBA OIL; CARNAUBA WAX; ALOE VERA LEAF; LAVENDER OIL; FRANKINCENSE OIL

MATY'S® ALL NATURAL Baby DIAPER RASH RELIEF

Active Ingredient

Zinc Oxide 1%

Purpose

Skin Protectant

Uses

• Helps treat and prevent diaper rash
• Protects chafed skin due to diaper rash and helps seal out wetness

Warnings:

For external use only

When using this product
• do not get into eyes

Stop use and ask a doctor if
• condition worsens
• symptoms last more than 7 days or clear up and occur again within a few days

Do not use on
• deep puncture wounds
• serious burns • animal bites

Keep out of reach of children
if swallowed get medical help or contact Poison Control Center.

Directions

• Apply as needed
• Clean and dry area before use. Apply liberally as needed to your baby’s bottom with each diaper change to create a moisture barrier that protects your baby’s skin.
• Change wet and soiled diapers promptly

Other Information

Store at room temperature.

Inactive Ingredients

Olive (Olea Europaea) Oil, Coconut (Cocos Nucifera) Oil, Castor (Ricinus Communis) Oil, Beeswax (Cera Alba), Jojoba (Simmondsia Chinensis) Oil, Carnauba Wax (Copernicia Cerifera), Aloe (Aloe Barbadensis) Extract, Lavender (Lavandula Angustifolia) Oil, Frankincense (Boswellia Carterii) Oil

Questions?

1-888-900-6289

ALL NATURAL

TREATS & PREVENTS DIAPER RASH

NATURALLY SOOTHES & CALMS

FRANKINCENSE & ALOE

FOR BABIES 2 MO. +OLDER

WE CURATE OUR INGREDIENTS FROM MOTHER NATURE'S CUPBOARD.

Our all natural ingredients may be harvested or mined and then purified.

NO PETROLEUM • NO PARABENS • NO PHTHALATES
NO FRAGRANCES • NO HYDROGENATED OILS

Pediatrician Tested

Gluten Free

No Animal Testing

Distributed By
Maty's Healthy Products, LLC
Boulder, CO 80301
888-900-6289 · matys.com

MADE IN AMERICA
WITH GLOBAL INGREDIENTS

vitamin angels®

We donate a portion of every sale to Vitamin Angels